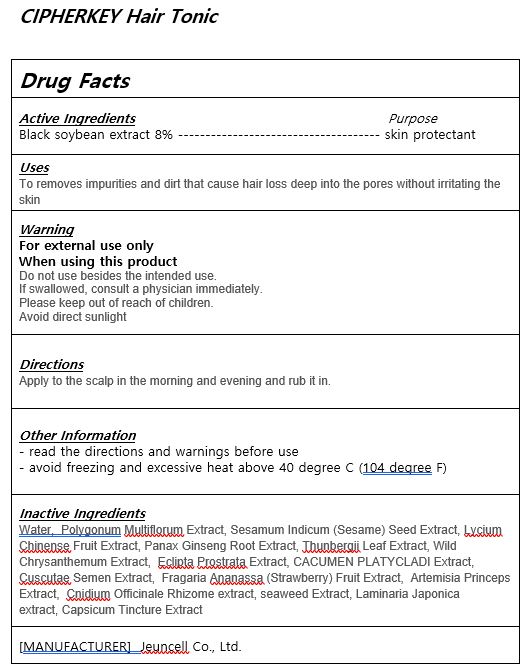 DRUG LABEL: CIPHERKEY HAIR TONIC
NDC: 54296-0002 | Form: LIQUID
Manufacturer: Jeuncell Co.,Ltd
Category: otc | Type: HUMAN OTC DRUG LABEL
Date: 20230922

ACTIVE INGREDIENTS: SOYBEAN OIL 8 g/100 mL
INACTIVE INGREDIENTS: WATER; PANAX GINSENG ROOT OIL

ACTIVE INGREDIENT

black soybean extracts

INACTIVE INGREDIENT

Water, Polygonum Multiflorum Extract, Sesamum Indicum (Sesame) Seed Extract, Lycium Chinense Fruit Extract, Panax Ginseng Root Extract, Thunbergii Leaf Extract, Wild Chrysanthemum Extract, Eclipta Prostrata Extract, CACUMEN PLATYCLADI Extract,
Cuscutae Semen Extract, Fragaria Ananassa (Strawberry) Fruit Extract, Artemisia Princeps Extract, Cnidium Officinale Rhizome extract, seaweed Extract, Laminaria Japonica extract, Capsicum Tincture Extract

PURPOSE

to clean scalp and norishment

Do not use besides the intended use.
If swallowed, consult a physician immediately.
Please keep out of reach of children.
Avoid direct sunlight

KEEP OUT OF REACH OF CHILDREN

Please keep out of reach of children.

Uses

Apply to the scalp in the morning and evening and rub it in.

DOSAGE AND ADMINISTRATION

for external use only